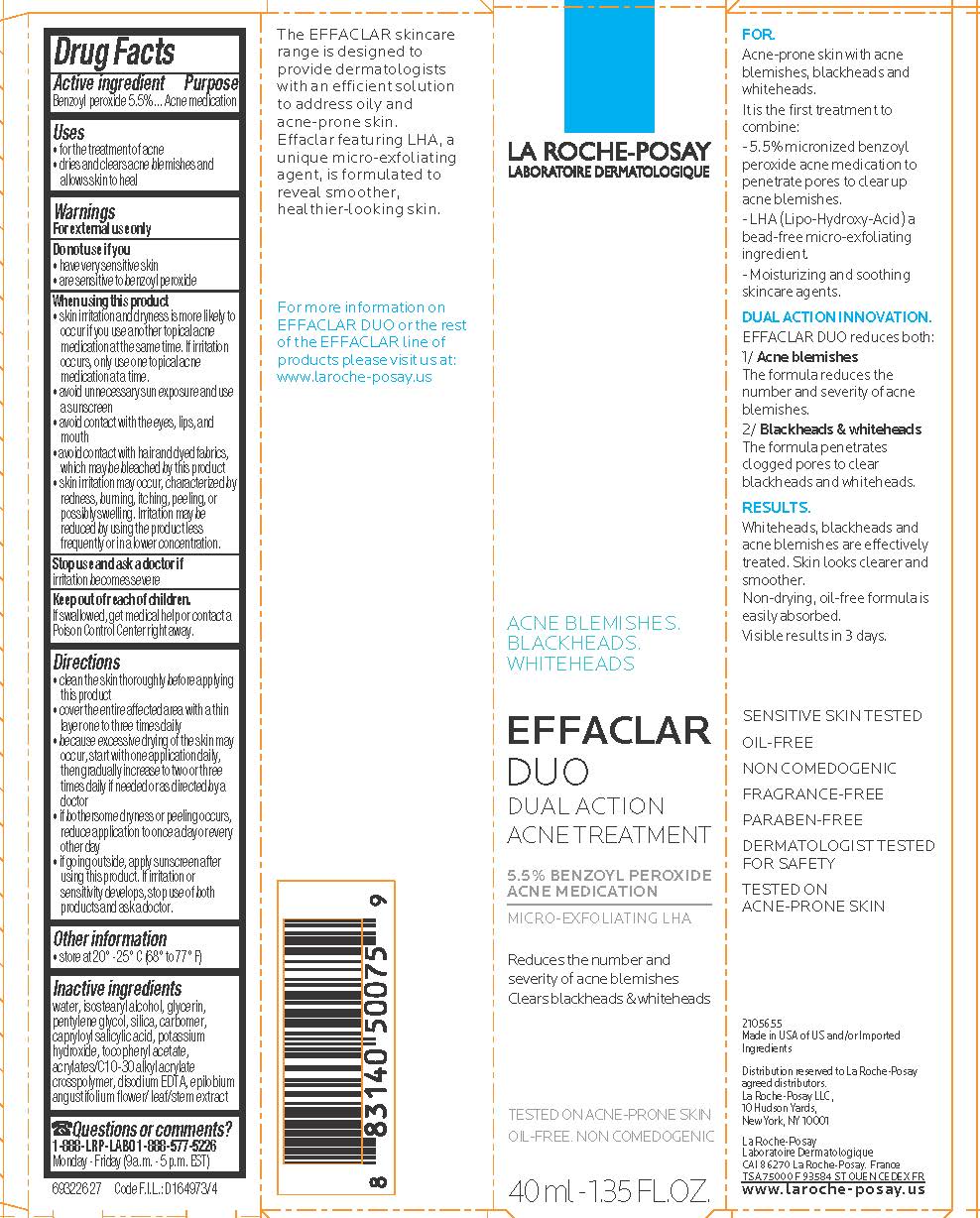 DRUG LABEL: La Roche Posay Laboratoire Dermatologique Effaclar Duo Acne Treatment
NDC: 49967-076 | Form: LOTION
Manufacturer: L'OREAL USA, INC.
Category: otc | Type: HUMAN OTC DRUG LABEL
Date: 20231231

ACTIVE INGREDIENTS: Benzoyl peroxide 55 mg/1 mL
INACTIVE INGREDIENTS: WATER; ISOSTEARYL ALCOHOL; GLYCERIN

Drug Facts

Active ingredient

Benzoyl peroxide 5.5%

Purpose

Acne medication

Uses

- for the treatment of acne
- dries and clears acne blemishes and allows skin to heal

Warnings

For external use only

Do not use if you

- have very sensitive skin
- are sensitive to benzoyl peroxide

When using this product

- skin irritation and dryness is more likely to occur if you use another topical acne medication at the same time. If irritation occurs, only use one topical acne medication at a time
- avoid unnecessary sun exposure and use a sunscreen
- avoid contact with the eyes, lips and mouth
- avoid contact with hair and dyed fabrics, which may be bleached by this product
- skin irritation may occur, characterized by redness, burning, itching, peeling, or possibly swelling. Irritation may be reduced by using the product less frequently or in a lower concentration.

Stop use and ask a doctor if

irritation becomes severe

Keep out of reach of children.

If swallowed, get medical help or contact a Poison Control Center right away.

Directions

- clean the skin thoroughly before applying this product
- cover the entire affected area with a thin layer one to three times daily
- because excessive drying of the skin may occur, start with one application daily, then gradually increase to two or three times daily if needed or as directed by a doctor
- if bothersome dryness or peeling occurs, reduce application to once a day or every other day
- if going outside, apply sunscreen after using this product. If irritation or sensitivity develops, stop use of both prdoucts and ask a doctor.

Other information

store at 20 - 25 C (68 to 77 F)

Inactive ingredients

water, isostearyl alcohol, glycerin, pentylene glycol, silica, carbomer, capryloyl salicylic acid, potassium hydroxide, tocopheryl acetate, acrylates/C10-30 alkyl acrylate crosspolymer, disodium EDTA, epilobium angustifolium flower/leaf/stem extract

Questions or comments?

1-888-LRP-LABO 1-888-577-5226

Monday - Friday (9 a.m. - 5 p.m. EST)